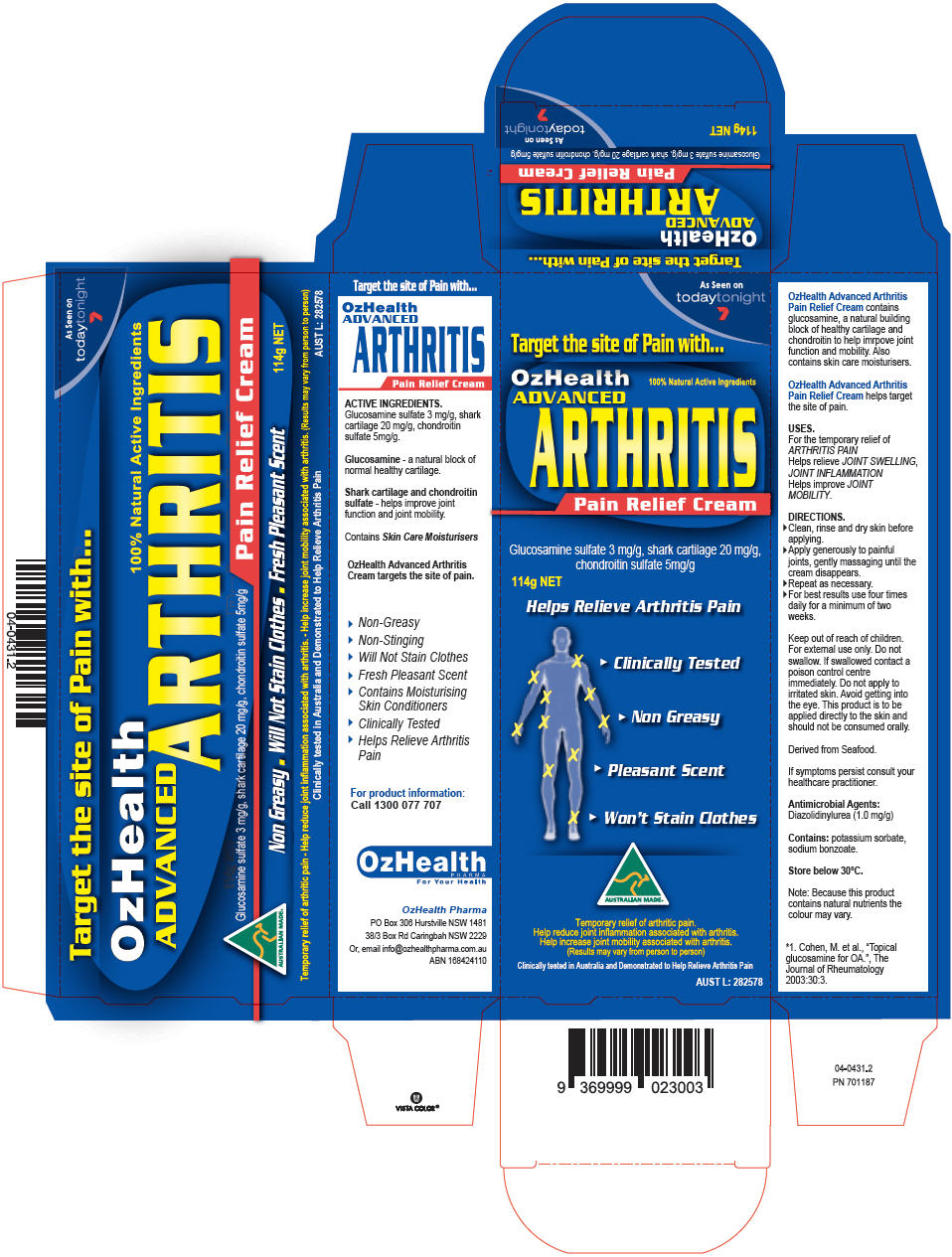 DRUG LABEL: OzHealth Advanced Arthritis
NDC: 64479-150 | Form: CREAM
Manufacturer: SmartScience Laboratories, Inc.
Category: otc | Type: HUMAN OTC DRUG LABEL
Date: 20180613

ACTIVE INGREDIENTS: Camphor (Synthetic) 5 mg/100 g
INACTIVE INGREDIENTS: Methyl Glucose Sesquistearate; Carbomer Interpolymer Type A (Allyl Sucrose Crosslinked); Alkyl (C12-15) Benzoate; Aloe Vera Leaf; Arnica Montana; Calcitriol; Carboxypolymethylene; Chondroitin Sulfate (Shark); Diazolidinyl Urea; Iodopropynyl Butylcarbamate; Dimethicone; Edetate Disodium Anhydrous; Panthenol; .Alpha.-Tocopherol Acetate; Escin; Glucosamine Sulfate Potassium Chloride; Glycerin; Glyceryl Monostearate; Hypromellose, Unspecified; Methyl Gluceth-20; Peppermint Oil; Potassium Hydroxide; Water; Shea Butter; Sorbitan Monolaurate

OzHealth ADVANCED ARTHRITIS Pain Relief Cream

PRINCIPAL DISPLAY PANEL - 114 g Tube Box

As Seen on
todaytonight
7

Target the site of Pain with...

OzHealth
ADVANCED
ARTHRITIS
Pain Relief Cream

100% Natural Active Ingredients

Glucosamine sulfate 3 mg/g, shark cartilage 20 mg/g,
chondroitin sulfate 5mg/g

114g NET

Helps Relieve Arthritis Pain

▶ Clinically Tested
▶ Non Greasy
▶ Pleasant Scent
▶ Won't Stain Clothes

AUSTRALIAN MADE®

Temporary relief of arthritic pain.
Help reduce joint inflammation associated with arthritis.
Help increase joint mobility associated with arthritis.
(Results may vary from person to person)

Clinically tested in Australia and Demonstrated to Help Relieve Arthritis Pain

AUST L: 282578